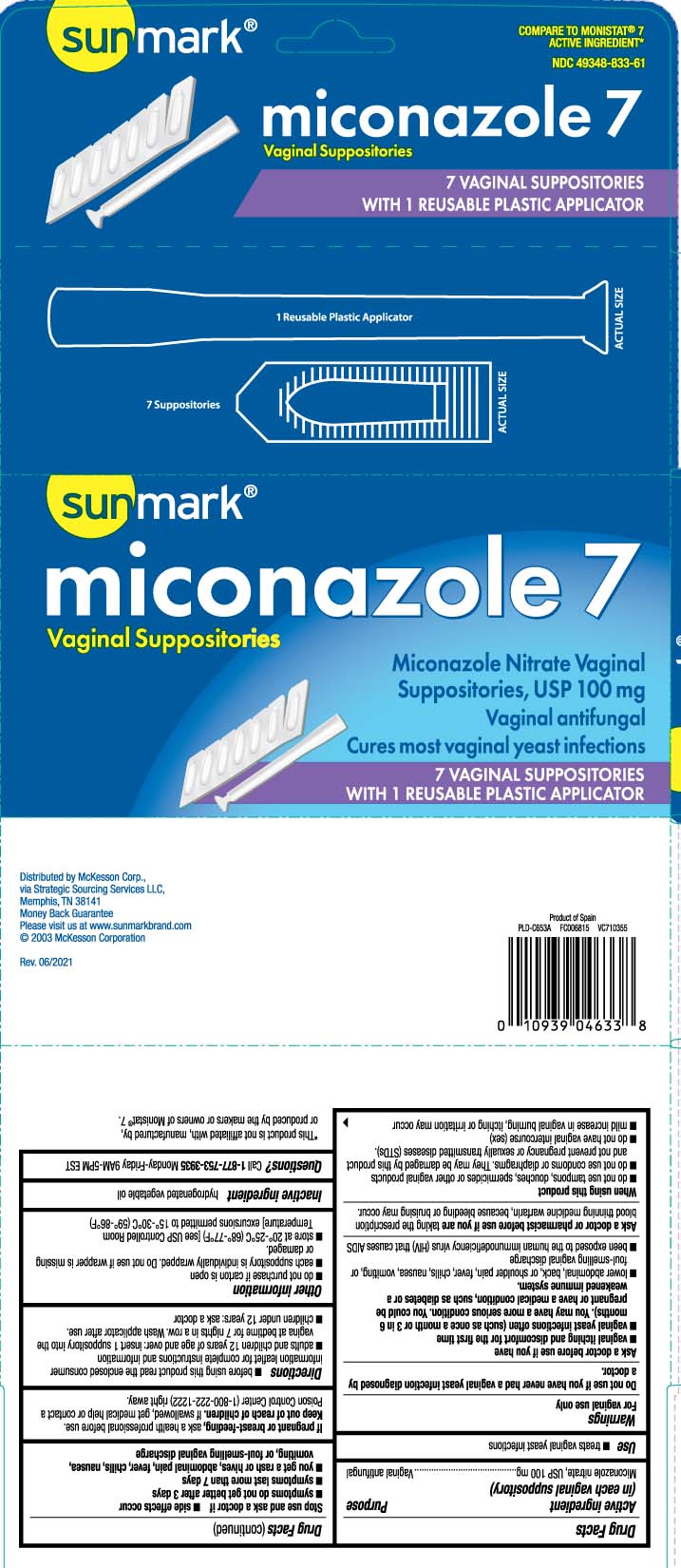 DRUG LABEL: Miconazole 7
NDC: 49348-833 | Form: SUPPOSITORY
Manufacturer: Strategic Sourcing Services LLC
Category: otc | Type: HUMAN OTC DRUG LABEL
Date: 20250909

ACTIVE INGREDIENTS: MICONAZOLE NITRATE 100 mg/1 1
INACTIVE INGREDIENTS: HYDROGENATED PALM KERNEL OIL; PALM KERNEL OIL

Miconazole Nitrate Vaginal Suppositories, USP

Active ingredient (in each vaginal suppository)

Miconazole nitrate, USP 100 mg

Purpose

Vaginal antifungal

Use

- treats vaginal yeast infections

Warnings

For vaginal use only

Do not use

if you have never had a vaginal yeast infection diagnosed by a doctor

Ask a doctor before use if you have

- vaginal itching and discomfort for the first time
- vaginal yeast infections often (such as once a month or 3 in 6 months). You may have a more serious condition. You could be pregnant or have a medical condition, such as diabetes or a weakened immune system.
- lower abdominal, back, or shoulder pain, fever, chills, nausea, vomiting, or foul-smelling vaginal discharge
- been exposed to the human immunodeficiency virus (HIV) that causes AIDS

Ask a doctor or pharmacist before use if you are

taking a prescription blood thinning medicine, such as warfarin, because bleeding or bruising may occur

When using this product

- do not use tampons, douches, spermicides or other vaginal products
- do not use condoms or diaphragms. They may be damaged by this product and not prevent pregnancy or sexually transmitted diseases (STDs).
- do not have vaginal intercourse (sex)
- mild increase in vaginal burning, itching or irritation may occur

Stop use and ask a doctor if

- side effects occur.
- symptoms do not get better after 3 days
- symptoms last more than 7 days
- you get a rash or hives, abdominal pain, fever, chills, nausea, vomiting, or foul-smelling vaginal discharge

If pregnant or breast-feeding,

ask a health professional before use.

Keep out of reach of children.

If swallowed, get medical help or contact a Poison Control Center (1-800-222-1222) right away.

Directions

- before using this product read the enclosed consumer information leaflet for complete instructions and information
- adults and children 12 years of age and over: insert 1 suppository into the vagina at bedtime for 7 nights in a row. Wash applicator after use.
- children under 12 years: ask a doctor

Other information

- do not purchase if carton is open
- each suppository is individually wrapped. Do not use if wrapper is missing or damaged.
- store at 20º-25ºC (68º-77ºF) [see USP Controlled Room Temperature] excursions permitted to 15º-30ºC (59º-86ºF).

Inactive ingredient

hydrogenated vegetable oil

Questions?

Call 1-877-753-3935 Monday-Friday 9AM-5PM EST

Principal display panel

COMPARETO MONISTAT® 7 ACTIVE INGREDIENT*

miconazole 7

Vaginal Suppositories

Miconazole Nitrate Vaginal

Suppositories, USP 100 mg

Vaginal antifungal

Cures most vaginal yeast infections

7 VAGINAL SUPPOSITORIES WITH 1 REUSABLE PLASTIC APPLICATOR

*This product is not affiliated with, manufactured by, or produced by the makers or owners of Monistat®

Distributed by McKesson Corp.,

via Strategic Sourcing Services LLC,

Memphis, TN 38141

www.sunmarkbrand.com

Package label

SUNMARK Vaginal Suppositories